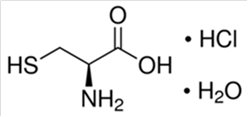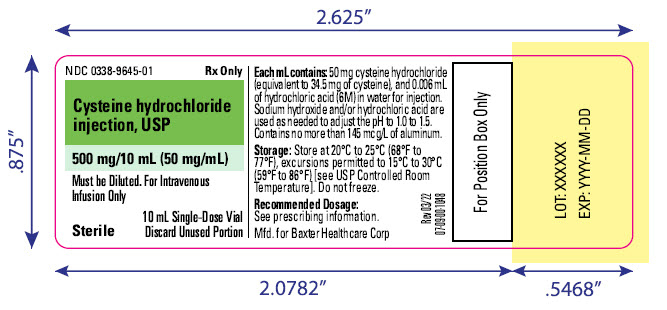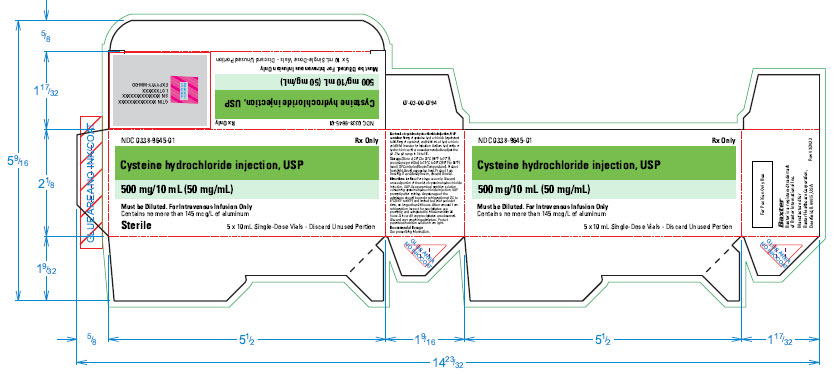 DRUG LABEL: CYSTEINE HYDROCHLORIDE
NDC: 0338-9645 | Form: INJECTION
Manufacturer: Baxter Healthcare Corporation
Category: prescription | Type: HUMAN PRESCRIPTION DRUG LABEL
Date: 20220429

ACTIVE INGREDIENTS: CYSTEINE HYDROCHLORIDE 34.5 mg/1 mL
INACTIVE INGREDIENTS: HYDROCHLORIC ACID 0.006 mL/1 mL; SODIUM HYDROXIDE; WATER

HIGHLIGHTS OF PRESCRIBING INFORMATION

These highlights do not include all the information needed to use cysteine hydrochloride injection, USP safely and effectively. See full prescribing information for cysteine hydrochloride injection, USP.
Cysteine hydrochloride injection, USP, for intravenous use
Initial U.S. Approval: 1971

1 INDICATIONS AND USAGE

Cysteine hydrochloride injection, USP is a sulfur-containing amino acid indicated for use as an additive to amino acids solutions to meet nutritional requirements of neonates (preterm and term infants less than one month of age) requiring total parenteral nutrition. (1)

2 DOSAGE AND ADMINISTRATION

- Cysteine hydrochloride injection, USP is for intravenous infusion after dilution and admixing only. (2.1)
- See full prescribing information for information on preparation, administration, and instructions for use. (2.1, 2.2, 2.3, 2.4)
- The recommended dosage in neonates is based upon the recommended daily protein (amino acid) requirements: 22 mg cysteine hydrochloride injection, USP/g amino acids. The corresponding volume is 0.44 mL cysteine hydrochloride injection, USP/g amino acids. (2.5)

3 DOSAGE FORMS AND STRENGTHS

Injection: 500 mg/10 mL (50 mg/mL) cysteine hydrochloride, USP in a single-dose vial. (3)

4 CONTRAINDICATIONS

- Hypersensitivity to one or more amino acids (4)
- Inborn errors of amino acid metabolism (4)
- Pulmonary edema or acidosis due to low cardiac output (4)

5 WARNINGS AND PRECAUTIONS

- Pulmonary Embolism due to Pulmonary Vascular Precipitates: If signs of pulmonary distress occur, stop the infusion and initiate a medical evaluation. (5.1)
- Vein Damage and Thrombosis: Solutions with osmolarity of 900 mOsm/L or more must be infused through a central catheter (2.1, 5.2)
- Increased Blood Urea Nitrogen (BUN): Monitor laboratory parameters and discontinue if BUN exceeds normal postprandial limits and continues to increase. (5.3)
- Acid-Base Imbalance: Monitor laboratory parameters and supplement with electrolytes as needed. (5.4)
- Hepatobiliary Disorders: Neurocognitive delay possible in infants; monitor liver function parameters and ammonia levels. (5.5, 8.4)
- Aluminum Toxicity: Increased risk in patients with renal impairment, including preterm infants. (5.6, 8.4)
- Monitoring and Laboratory Tests: Monitor fluid and electrolytes, serum osmolarity, blood glucose, kidney and liver function, blood count, and coagulation parameters throughout treatment. (5.7)

6 ADVERSE REACTIONS

Most common adverse reactions are local reactions (warm sensation, erythema, phlebitis, and thrombosis at the infusion site), generalized flushing, fever, nausea, and metabolic acidosis. (6)

To report SUSPECTED ADVERSE REACTIONS, contact Baxter Healthcare Corporation at 1-866-888-2472 or FDA at 1-800-FDA-1088 or www.fda.gov/medwatch.

FULL PRESCRIBING INFORMATION

1 INDICATIONS AND USAGE

Cysteine hydrochloride injection, USP is indicated for use as an additive to amino acids solutions to meet nutritional requirements of neonates (preterm and term infants less than one month of age) requiring total parenteral nutrition.

2 DOSAGE AND ADMINISTRATION

2.1 Important Administration Information

Cysteine hydrochloride injection, USP is for intravenous infusion after dilution and admixing use only. Prior to administration, cysteine hydrochloride injection, USP must be diluted and used as an admixture in parenteral nutrition solutions.

The resulting solution is for intravenous infusion into a central or peripheral vein. The choice of a central or peripheral venous route should depend on the osmolarity of the final infusate. Solutions with osmolarity of 900 mOsm/L or greater must be infused through a central catheter [see Warnings and Precautions (5.2)].

2.2 Preparation and Administration Information

- Prior to administration, cysteine hydrochloride injection, USP must be diluted and used as an admixture in parenteral nutrition solutions.
- Cysteine hydrochloride injection, USP is to be prepared only in a suitable work area such as a laminar flow hood (or an equivalent clean air compounding area). The key factor in the preparation is careful aseptic technique to avoid inadvertent touch contamination during mixing of solutions and addition of other nutrients.
- Cysteine hydrochloride injection, USP is for addition to amino acid solutions prior to further admixing with dextrose injection using a parenteral nutrition container.
- Calcium and phosphate ratios must be considered. Excess addition of calcium and phosphate, especially in the form of mineral salts, may result in the formation of calcium phosphate precipitates [see Warnings and Precautions (5.1)].
- Use a dedicated line for parenteral nutrition solutions.
- Intravenous lipid emulsions can be infused concurrently into the same vein as cysteine hydrochloride injection, USP-containing amino acid and dextrose solutions by a Y-connector located near the infusion site; flow rates of each solution should be controlled separately by infusion pumps.
- For administration, use a 0.22 micron in-line filter.
- To prevent air embolism, use a non-vented infusion set or close the vent on a vented set, avoid multiple connections, do not connect flexible containers in series, fully evacuate residual gas in the container prior to administration, do not pressurize the flexible container to increase flow rates, and if administration is controlled by a pumping device, turn off pump before the container runs dry.
- Visually inspect the diluted parenteral nutrition solution containing cysteine hydrochloride injection, USP for particulate matter and discoloration before admixing, after admixing, after removal from refrigeration, and prior to administration. The solution should be clear and there should be no precipitates. A slight yellow color does not alter the quality and efficacy of this product.

2.3 Preparation Instructions for Admixing Using a Parenteral Nutrition Container

- Remove cysteine hydrochloride injection, USP vial from the carton and inspect for particulate matter.
- Transfer the required amount of cysteine hydrochloride injection, USP to an amino acid solution using strict aseptic techniques to avoid microbial contamination.
- The amino acid solution containing cysteine hydrochloride injection, USP can then be used to prepare admixtures in the parenteral nutrition container using strict aseptic techniques.
- Amino acids solution containing cysteine hydrochloride injection, USP may be mixed with dextrose injection. The following proper mixing sequence must be followed to minimize pH related problems:
  1. Transfer dextrose injection to the parental nutrition pooling container
  2. Transfer phosphate salt
  3. Transfer cysteine hydrochloride injection, USP-containing amino acid solution
  4. Transfer electrolytes
  5. Transfer trace elements
- Use gentle agitation during admixing to minimize localized concentration effects; shake containers gently after each addition.
- For automated compounding, refer to Instructions for Use of the applicable compounder.
- Because additives may be incompatible, evaluate all additions to the parenteral nutrition container for compatibility and stability of the resulting preparation. Consult with pharmacist, if available. Questions about compatibility may be directed to Baxter Healthcare Corporation. If it is deemed advisable to introduce additives to the parenteral nutrition container, use aseptic technique.
- Inspect the final parenteral nutrition solution containing cysteine hydrochloride injection, USP to ensure that precipitates have not formed during mixing or on addition of additives. Discard if any precipitates are observed.

Stability and Storage

- For single use only. Discard unused portion of the vial of cysteine hydrochloride injection, USP.
- Use parenteral nutrition solution containing cysteine hydrochloride injection, USP promptly after mixing. Any storage of the admixture should be under refrigeration at 2ºC to 8ºC (36ºF to 46ºF) and limited to a brief period of time, no longer than 24 hours. After removal from refrigeration, inspect for precipitates, use promptly, and complete the infusion within 24 hours. Discard if any precipitates are observed.
- Discard any remaining admixture.
- Protect parenteral nutrition solution from light.

2.4 Dosing Considerations

The dosage of the final parenteral nutrition solution containing cysteine hydrochloride injection, USP must be based on the concentrations of all components in the solution and the recommended nutritional requirements [see Dosage and Administration (2.5)]. Consult the prescribing information of all added components to determine the recommended nutritional requirements.

The dosage of cysteine hydrochloride injection, USP should be individualized based on the patient’s clinical condition (ability to adequately metabolize amino acids), body weight and nutritional/fluid requirements, as well as additional energy given orally/enterally to the patient. Prior to initiating parenteral nutrition, the following patient information should be reviewed: review of all medications, gastrointestinal function and laboratory data (such as electrolytes (including magnesium, calcium, and phosphorus), glucose, urea/creatinine, liver panel, and complete blood count.

Prior to administration of parenteral nutrition solution containing cysteine hydrochloride injection, USP, correct severe fluid, electrolyte and acid-base disorders.

2.5 Recommended Dosage for Neonates

The recommended dosage and volume of cysteine hydrochloride injection, USP is based upon the recommended daily protein (amino acid) requirements.

Table 1. Recommended Daily Dosage of cysteine hydrochloride injection, USP in Neonates (Preterm and Term Infants Less Than One Month of Age)

Dosage | Protein [Protein is provided as amino acids.] Requirement (g Amino Acids/kg/day)^1 | Dosage (mg cysteine hydrochloride injection, USP/g Amino Acids) | Volume (mL cysteine hydrochloride injection, USP/g Amino Acids)
Neonates | 3 to 4 | 22 | 0.44

Cysteine hydrochloride injection, USP contains 50 mg/mL of cysteine hydrochloride (equivalent to 34.5 mg/mL of cysteine). Therefore, the recommended dosage of cysteine hydrochloride injection, USP provides 15 mg cysteine/gram of amino acids for neonates.

3 DOSAGE FORMS AND STRENGTHS

Injection: 500 mg/10 mL (50 mg/mL) cysteine hydrochloride, USP as a clear, colorless, sterile solution in a single-dose vial.

4 CONTRAINDICATIONS

Cysteine hydrochloride injection, USP is contraindicated in:

- Patients with known hypersensitivity to one or more amino acids.
- Patients with inborn errors of amino acid metabolism due to risk of severe metabolic or neurologic complications.
- Patients with pulmonary edema or acidosis due to low cardiac output.

5 WARNINGS AND PRECAUTIONS

5.1 Pulmonary Embolism due to Pulmonary Vascular Precipitates

Pulmonary vascular precipitates causing pulmonary vascular emboli and pulmonary distress have been reported in patients receiving parenteral nutrition. In some fatal cases, pulmonary embolism occurred as a result of calcium phosphate precipitates. Precipitation following passage through an in-line filter and suspected in vivo precipitate formation has also been reported. If signs of pulmonary distress occur, stop the parenteral nutrition infusion and initiate a medical evaluation. In addition to inspection of the solution [see Dosage and Administration (2.1, 2.2)], the infusion set and catheter should also periodically be checked for precipitates.

5.2 Vein Damage and Thrombosis

Cysteine hydrochloride injection, USP must be diluted and used as an admixture in parenteral nutrition solutions. Solutions with an osmolarity of 900 mOsm/L or greater must be infused through a central catheter [see Dosage and Administration (2.1)]. The infusion of hypertonic nutrient injections into a peripheral vein may result in vein irritation, vein damage, and/or thrombosis. The primary complication of peripheral access is venous thrombophlebitis, which manifests as pain, erythema, tenderness or a palpable cord. Remove the catheter as soon as possible, if thrombophlebitis develops.

5.3 Increased Blood Urea Nitrogen (BUN)

Intravenous infusion of amino acids may induce a rise in blood urea nitrogen (BUN), especially in patients with impaired hepatic or renal function. Appropriate laboratory tests should be performed periodically and infusion discontinued if BUN levels exceed normal postprandial limits and continue to rise. It should be noted that a modest rise in BUN normally occurs as a result of increased protein intake.

Administration of amino acid solutions in the presence of impaired renal function may augment an increasing BUN, as does any protein dietary component.

5.4 Acid-Base Imbalance

Administration of cysteine hydrochloride injection, USP may result in metabolic acidosis in neonates.

Administration of amino acid solutions to a patient with hepatic impairment may result in serum amino acid imbalances, metabolic alkalosis, prerenal azotemia, hyperammonemia, stupor and coma.

Frequent clinical evaluation and laboratory determinations are necessary for proper monitoring of acid-base balance during parenteral nutrition therapy. Significant deviations from normal concentrations may require the use of additional electrolyte supplements.

5.5 Hepatobiliary Disorders

Hepatobiliary disorders are known to develop in some patients, including neonates, without preexisting liver disease who receive parenteral nutrition, including cholecystitis, cholelithiasis, cholestasis, hepatic steatosis, fibrosis and cirrhosis, possibly leading to hepatic failure. The etiology of these disorders is thought to be multifactorial and may differ between patients.

Instances of asymptomatic hyperammonemia have been reported in patients receiving parenteral nutrition without overt liver dysfunction. The mechanisms of this reaction are not clearly defined but may involve genetic defects and immature or subclinically impaired liver function [see Contraindications (4), Use in Specific Populations (8.4)]

Hyperammonemia is of special significance in infants, as it can result in neurocognitive delays. Monitor liver function parameters and ammonia levels during treatment with cysteine hydrochloride injection, USP. Patients developing signs of hepatobiliary disorders should be assessed early by a clinician knowledgeable in liver diseases in order to identify possible causative and contributory factors, and possible therapeutic and prophylactic interventions.

5.6 Aluminum Toxicity

Cysteine hydrochloride injection, USP contains aluminum that may be toxic.

Aluminum may reach toxic levels with prolonged parenteral administration in patients with renal impairment. Neonates and preterm infants are particularly at risk for aluminum toxicity because their kidneys are immature, and they require large amounts of calcium and phosphate solutions, which also contain aluminum.

Patients with renal impairment including neonates and preterm infants, who receive greater than 4 to 5 mcg/kg/day of parenteral aluminum can accumulate aluminum to levels associated with central nervous system and bone toxicity. Tissue loading may occur at even lower rates of administration.

Exposure to aluminum from cysteine hydrochloride injection, USP is not more than 0.25 mcg/kg/day when preterm and term neonates are administered the recommended maximum dosage of cysteine hydrochloride injection, USP (22 mg cysteine hydrochloride/g of amino acids and 4 g of amino acids/kg/day) [see Dosage and Administration (2.5)]. When prescribing cysteine hydrochloride injection, USP for use in parenteral nutrition containing other small volume parenteral products, the total daily patient exposure to aluminum from the admixture should be considered and maintained at no more than 5 mcg/kg/day [see Use in Specific Populations (8.4)].

5.7 Monitoring and Laboratory Tests

Monitor fluid and electrolyte status, serum osmolarity, blood glucose, liver and kidney function, ammonia levels, blood count and coagulation parameters throughout treatment [see Dosage and Administration (2.4)].

6 ADVERSE REACTIONS

The following serious adverse reactions are discussed in greater detail in other sections of the prescribing information:

- Pulmonary embolism due to pulmonary vascular precipitates [see Warnings and Precautions (5.1)]
- Vein damage and thrombosis [see Warnings and Precautions (5.2)]
- Increased BUN [see Warnings and Precautions (5.3)]
- Acid-base imbalance [see Warnings and Precautions (5.4)]
- Hepatobiliary disorders [see Warning and Precautions (5.5)]
- Aluminum toxicity [see Warnings and Precautions (5.6)]

Adverse reactions with the use of cysteine hydrochloride injection were identified in clinical studies or postmarketing reports. Because these reactions are reported voluntarily from a population of uncertain size, it is not always possible to estimate their frequency reliably or to establish a causal relationship to drug exposure.

- Metabolic acidosis
- Local infusion site reactions, including a warm sensation, erythema, phlebitis, and thrombosis at the infusion site
- Generalized flushing, fever, and nausea

8 USE IN SPECIFIC POPULATIONS

8.1 Pregnancy

Risk Summary

Cysteine hydrochloride injection, USP for use as an additive to amino acid solutions to meet nutritional requirements is not indicated for use in adults. Appropriate administration of cysteine hydrochloride injection, USP is not expected to cause major birth defects, miscarriage or adverse maternal or fetal outcomes. Animal reproduction studies have not been conducted with cysteine hydrochloride.

8.2 Lactation

Risk Summary

Cysteine hydrochloride injection, USP is used as an additive to amino acid solutions to meet nutritional requirements of neonates requiring total parenteral nutrition and is not indicated for use in adults. There are no data on the presence of cysteine hydrochloride in human or animal milk or the effects on milk production. Data available on the effects of cysteine hydrochloride on infants, either directly or through breastmilk, do not suggest a significant risk of adverse reactions from exposure.

8.4 Pediatric Use

Cysteine hydrochloride injection, USP is indicated for use as an additive to amino acid solutions to meet the nutritional requirements of neonates, including preterm infants, requiring total parenteral nutrition. The safety profile for cysteine hydrochloride injection, USP use in neonates includes risks of acid-base imbalance and hepatobiliary dysfunction.

Acid-base imbalance, including metabolic acidosis, and liver dysfunction may occur with cysteine hydrochloride injection, USP administration in preterm infants. Frequent clinical and laboratory assessments are necessary to monitor and manage fluid balance, electrolyte concentrations, liver tests, and acid-base balance during parenteral nutrition therapy [see Warnings and Precautions (5.4)].

Hyperammonemia is of special significance in neonates. This reaction appears to be related to a deficiency of the urea cycle amino acids of genetic or product origin. It is essential that blood ammonia be measured during treatment [see Warnings and Precautions (5.5)].

Because of immature renal function, neonates including preterm infants, receiving prolonged parenteral nutrition with cysteine hydrochloride injection, USP may be at higher risk of aluminum toxicity [see Warnings and Precautions (5.7)].

10 OVERDOSAGE

In the event of over hydration or solute overload, re-evaluate the patient and institute appropriate corrective measures [see Warnings and Precautions (5.3, 5.4, 5.5, 5.7)].

11 DESCRIPTION

Cysteine hydrochloride injection, USP (cysteine hydrochloride injection) is a sterile, nonpyrogenic solution for intravenous use supplied as 500 mg/10 mL cysteine hydrochloride, USP in a single-dose vial.

Each mL of cysteine hydrochloride injection, USP contains 50 mg of cysteine hydrochloride, (equivalent to 34.5 mg of cysteine), and 0.006 mL of hydrochloric acid (6M) in water for injection. Sodium hydroxide and/or hydrochloric acid are used as needed to adjust the pH. The pH range of cysteine hydrochloride injection, USP is 1.0 to 1.5.

The active ingredient is cysteine hydrochloride. The chemical name of cysteine hydrochloride is L-cysteine hydrochloride monohydrate. Its molecular formula is C3H7NO2S • HCI • H2O and molecular weight is 175.63. The chemical structure of L-cysteine hydrochloride monohydrate is depicted below:

Cysteine hydrochloride is a white crystalline powder soluble in water. Cysteine is a sulfur-containing amino acid and is prone to oxidation when exposed to air in aqueous solution, which may convert cysteine to insoluble cystine resulting in precipitation over time.

Cysteine hydrochloride injection, USP contains no more than 145 mcg/L of aluminum.

12 CLINICAL PHARMACOLOGY

12.1 Mechanism of Action

Endogenous cysteine is synthesized from methionine by the enzyme, cystathionase, via the trans-sulfuration pathway, and serves as a precursor substrate for both glutathione and taurine. Cysteine hydrochloride injection, USP provides cysteine to the systemic circulation of neonates who require parenteral nutrition and cannot synthesize adequate quantities of cysteine due to deficient cystathionase activity.

15 REFERENCES

1. Ayers P. et al. A.S.P.E.N. Parenteral Nutrition Handbook, 2nd ed. 2014 pg. 123 and 124.

16 HOW SUPPLIED/STORAGE AND HANDLING

Cysteine hydrochloride injection, USP (cysteine hydrochloride injection) is a clear, colorless, sterile and nonpyrogenic solution supplied as follows:

500 mg/10 mL (50 mg/mL) of cysteine hydrochloride, USP in single-dose vials (NDC 0338-
9645-01), packaged as 5 vials per carton (NDC 0338-9645-01)

Store cysteine hydrochloride injection, USP at 20°C to 25°C (68°F to 77°F); excursions
permitted to 15°C to 30°C (59°F to 86°F) [see USP Controlled Room Temperature].

Protect from light. Avoid excessive heat. Protect from freezing. If accidentally frozen, discard
the vial.

Vial stoppers are not made with natural rubber latex.

For storage of admixed solution see Dosage and Administration (2.3)

17 PATIENT COUNSELING INFORMATION

Inform caregivers or home healthcare providers of the following risks of cysteine hydrochloride injection, USP:

- Pulmonary embolism due to pulmonary vascular precipitates [see Warnings and Precautions (5.1)]
- Vein damage and thrombosis [see Warnings and Precautions (5.2)]
- Increased BUN [see Warnings and Precautions (5.3)]
- Acid-base imbalance [see Warnings and Precautions (5.4)]
- Hepatobiliary disorders [see Warning and Precautions (5.5)]
- Aluminum toxicity [see Warnings and Precautions (5.6)]
- Monitoring and laboratory tests [see Warnings and Precautions (5.7)]

Manufactured for:

Baxter Healthcare Corporation,

Deerfield, IL 60015, USA

Baxter is a registered trademark of Baxter International Inc.

Rev. 04/22

07-19-00-4043

PACKAGE/LABEL PRINCIPAL DISPLAY PANEL

NDC 0338-9645-01

Rx only

Cysteine hydrochloride injection, USP

500 mg/10 mL (50 mg/mL)

Must be Diluted. For Intravenous
Infusion Only

Sterile

10 mL Single-Dose Vial
Discard Unused Portion

Each mL contains: 50 mg cysteine hydrochloride
(equivalent to 34.5 mg of cysteine), and 0.006 mL
of hydrochloric acid (6M) in water for injection.
Sodium hydroxide and/or hydrochloric acid are
used as needed to adjust the pH to 1.0 to 1.5.
Contains no more than 145 mcg/l of aluminum.

Storage: Store at 20°C to 25°C (68°F to
77°F), excursions permitted to 15° to 30°C
(59°F to 86°F) [see USP Controlled Room
Temperature]. Do not freeze.

Recommended Dosage:
See prescribing information.
Mfd. for Baxter Healthcare Corp

Rev 03/22

07-09-00-1048

For Position Box Only

LOT: XXXXXX
EXP: YYYY-MM-DD

NDC 0338-9645-01

Rx Only

Cysteine hydrochloride injection, USP

500 mg/10 mL (50 mg/mL)

Must be Diluted. For Intravenous Infusion Only

5 x 10 mL Single-Dose Vials – Discard Unused Portion

Reserved for 2D barcode

GTIN XXXXXXXXXXXXXX
SN XXXXXXXXXXXXXX
LOT XXXXXX
EXP YYY-MD-DD

NDC 0338-9645-01

Rx Only

Cysteine hydrochloride injection, USP

500 mg/10 mL (50 mg/mL)

Must be Diluted. For Intravenous Infusion Only
Contains no more than 145 mcg/L of aluminum

Sterile

5 x 10 mL Single-Dose Vials – Discard Unused Portion

07-03-00-0794

Each mL of cysteine hydrochloride injection, USP
contains: 50mg of cysteine hydrochloride (equivalent
to 34.5 mg of cysteine), and 0.006 mL of hydrochloric
acid (6M) in water for injection. Sodium hydroxide or
hydrochloric acid are used as needed to adjust the
pH. The pH range is 1.0 to 1.5.

Storage: Store at 20°C to 25°C (68°F to 77°F),
excursions permitted to 15°C to 30°C (59°F to 86°F)
[see USP Controlled Room Temperature]. Protect
from light. Avoid excessive heat. Protect from
freezing. If accidently frozen, discard the vial.

Directions for Use: For single use only. Discard
unused portion of the vial of cysteine hydrochloride
injection, USP. Use parenteral nutrition solution
containing cysteine hydrochloride injection, USP
promptly after mixing. Any storage of the
admixture should be under refrigeration at 2°C to
8°C (36°F to 46°F) and limited to brief period of
time, no longer than 24 hours. After removal from
refrigeration, inspect for precipitates, use
promptly, and complete the infusion within 24
hours. Discard if any precipitates are observed.
Discard any remaining admixture. Protect
parenteral nutrition solution from light.

Recommended Dosage:
See prescribing information.

NDC 0338-9645-01

Cysteine hydrochloride injection, USP

500 mg/10 mL (50 mg/mL)

Must be Diluted. For Intravenous Infusion Only
Contains no more than 145 mcg/L of aluminum

5 x 10 mL Single-Dose Vials- Discard Unused Portion

For Position Only Box

Baxter

Baxter is a registered trademark
of Baxter International Inc.
Manufactured for
Baxter Healthcare Corporation,
Deerfield, IL 60015, USA

Rev 03/2022